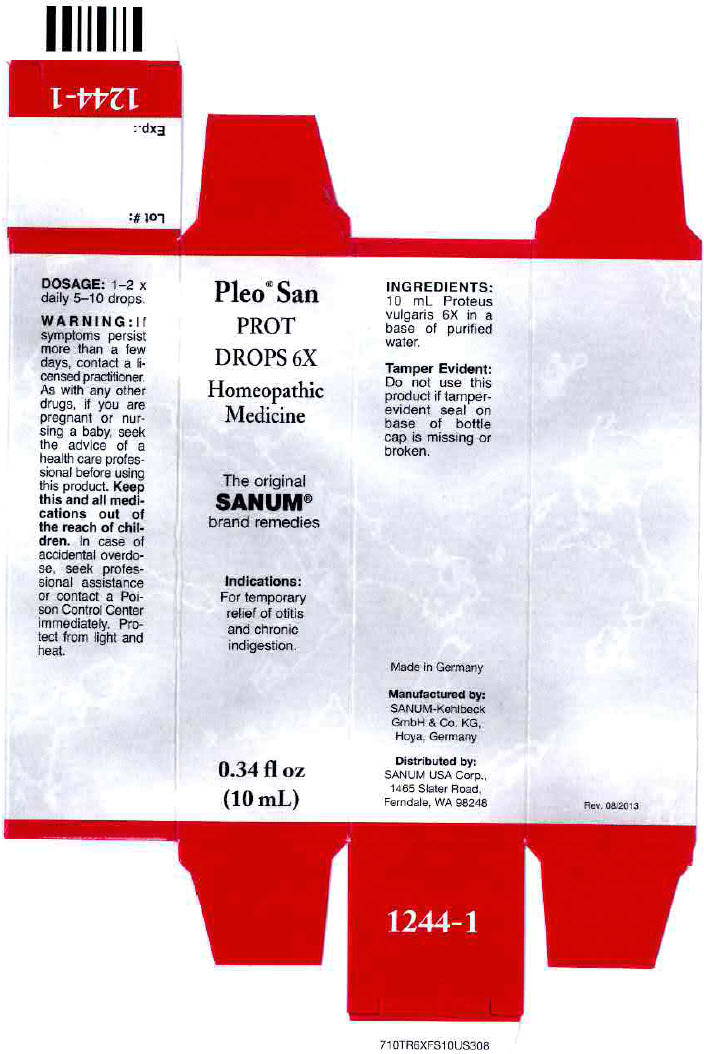 DRUG LABEL: Pleo San Prot
NDC: 60681-1244 | Form: SOLUTION/ DROPS
Manufacturer: Sanum Kehlbeck GmbH & Co. KG
Category: homeopathic | Type: HUMAN OTC DRUG LABEL
Date: 20131030

ACTIVE INGREDIENTS: proteus vulgaris 6 [hp_X]/10 mL
INACTIVE INGREDIENTS: water

Pleo™ San
PROT
DROPS 6X

PURPOSE

Homeopathic Medicine

0.34 fl oz
(10 mL)

Indications

For temporary relief of otitis and chronic indigestion.

INGREDIENTS

INACTIVE INGREDIENT

10 mL Proteus vulgaris 6X in a base of purified water.

Tamper Evident

Do not use this product if tamper-evident seal on base of bottle cap is missing or broken.

DOSAGE

1-2 × daily 5-10 drops.

WARNING

If symptoms persist more than a few days, contact a licensed practitioner. As with any other drugs, if you are pregnant or nursing a baby, seek the advice of a health care professional before using this product.

KEEP OUT OF REACH OF CHILDREN

Keep this and all other medications out of the reach of children. In case of accidental overdose, seek professional assistance or contact a Poison Control Center immediately.

STORAGE AND HANDLING

Protect from light and heat.

Made in Germany

Distributed by:
SANUM USA Corp.
1465 Slater Road
Ferndale, WA 98248

Manufactured By:
Sanum-Kehlbeck,
GmbH & Co. KG

Rev. 12/2005

PRINCIPAL DISPLAY PANEL - 10 mL Bottle Carton

Pleo® San

PROT
DROPS 6X

Homeopathic
Medicine

The original
SANUM®
brand remedies

Indications:
For temporary
relief of otitis
and chronic
indigestion.

0.34 fl oz
(10 mL)